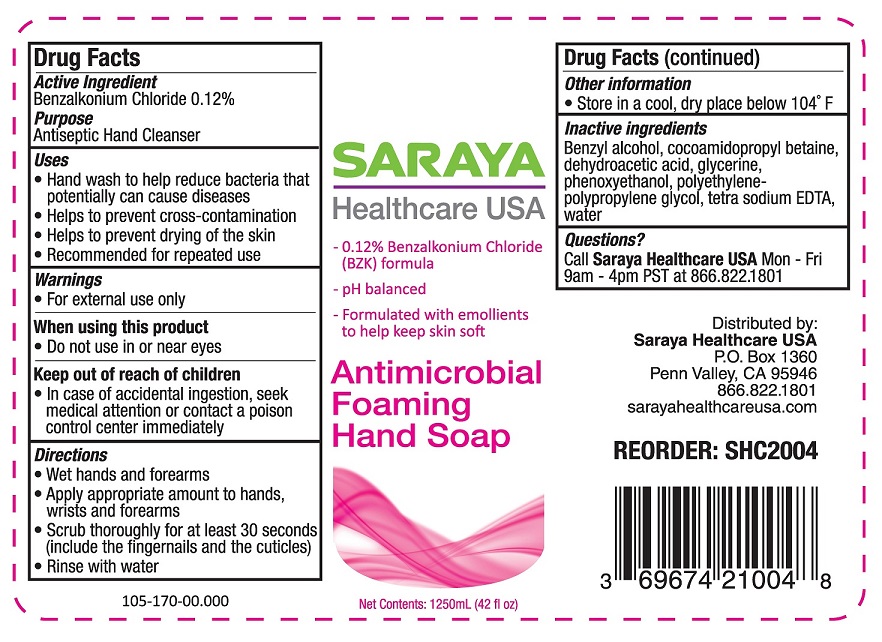 DRUG LABEL: Antimicrobial Foaming Hand Sanitizer
NDC: 69674-210 | Form: LIQUID
Manufacturer: Saraya Healthcare
Category: otc | Type: HUMAN OTC DRUG LABEL
Date: 20260113

ACTIVE INGREDIENTS: BENZALKONIUM CHLORIDE 0.12 mg/100 mL
INACTIVE INGREDIENTS: PHENOXYETHANOL; POLYETHYLENE GLYCOL, UNSPECIFIED; WATER; GLYCERIN; EDETIC ACID; DEHYDROACETIC ACID; BENZYL ALCOHOL; COCAMIDOPROPYL BETAINE

SARAYA ANTIMICROBIAL FOAMING HAND SOAP 69674-210

Active Ingredient

Benzalkonium Chloride 0.12%

Purpose

Antiseptic Hand Cleanser

Uses

- Hand wash to help reduce bacteria that potentially can cause diseases
- Helps to prevent cross-contamination
- Helps to prevent drying of the skin
- Recommended for repeated use

Warnings

- For external use only

When using this product

- Do not use in or near the eyes

Keep out of reach of children.

- In case of accidental ingestion, seek medical attention or contact a Poison Control Center immediately.

Directions

- Wet hands and forearms
- Apply appropriate amount to hands, wrists, and forearms
- Scrub thoroughly for at least 30 seconds (include the fingernails and the cuticles)
- Rinse with water

Other information

- Store in a cool, dry place below 104°F

Inactive ingredients

Benzyl alcohol, cocoamidopropyl betaine, dehydroacetic acid, glycerine, phenoxyethanol, polyethylene-propylene glycol, tetra-sodium EDTA, water

Questions?

Call Saraya Healthcare USAMon - Fri

9am - 4pm PST at 888.822.1801

Distributed by:

Saraya Healthcare USA

P.O. Box 1360

Penn Valley, CA 95946

866.822.1801

sarayahealthcareusa.com

SARAYAHealthcare USA

– 0.12% Benzalkonium Chloride (BZK) formula

– pH balanced

– Formulated with emollients to help keep skin soft

Antimicrobial Foaming Hand Soap

Net Contents: 1250mL (42 fl oz)